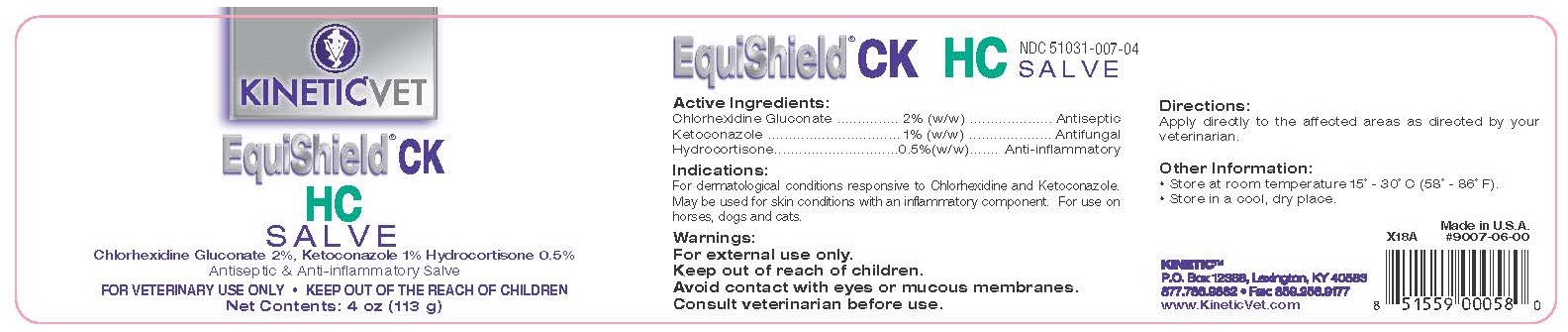 DRUG LABEL: EquiShield CK HC
NDC: 51031-007 | Form: SALVE
Manufacturer: Kinetic Technologies, LLC
Category: animal | Type: OTC ANIMAL DRUG LABEL
Date: 20231127

ACTIVE INGREDIENTS: CHLORHEXIDINE GLUCONATE 2 g/100 g; KETOCONAZOLE 1 g/100 g; HYDROCORTISONE 0.5 g/100 g

EquiShield CK HC Salve

Active Ingredients:

Chlorhexidine Gluconate .......... 2% (w/w) ................. Antiseptic
Ketoconazole .......................... 1% (w/w) .................Antifungal
Hydrocortisone ......................0.5% (w/w) ......Anti-inflammatory

Indications:

For dermatological conditions responsive to Chlorhexidine and Ketoconazole. May be used for skin conditions with an inflammatory component. For use on horses, dogs and cats.

Warnings:

For external use only.

Keep out of reach of children.

Avoid contact with eyes or mucous membranes.

Consult veterinarian before use.

Directions:

Apply directly to the affected areas as directed by your veterinarian.

Other Information:

• Store at room temperature 15˚ - 30˚C (58˚ - 86˚F).
• Store in a cool, dry place.

NDC 51031-007-04

Made in the U.S.A.

#9007-06-00

KINETIC™

P.O. Box 12388, Lexington, KY 40538

877.786.9882 • FAx: 859.258.9177

www.KineticVet.com

KINETIC™VET

EquiShield® CK HC SALVE

Chlorhexidine Gluconate 2%, Ketoconazole 1%, Hydrocortisone 0.5%

Antiseptic & Anti-inflammatory Salve

FOR VETERINARY USE ONLY • KEEP OUT OF REACH OF CHILDREN

Net Contents: 4 oz (113 g)